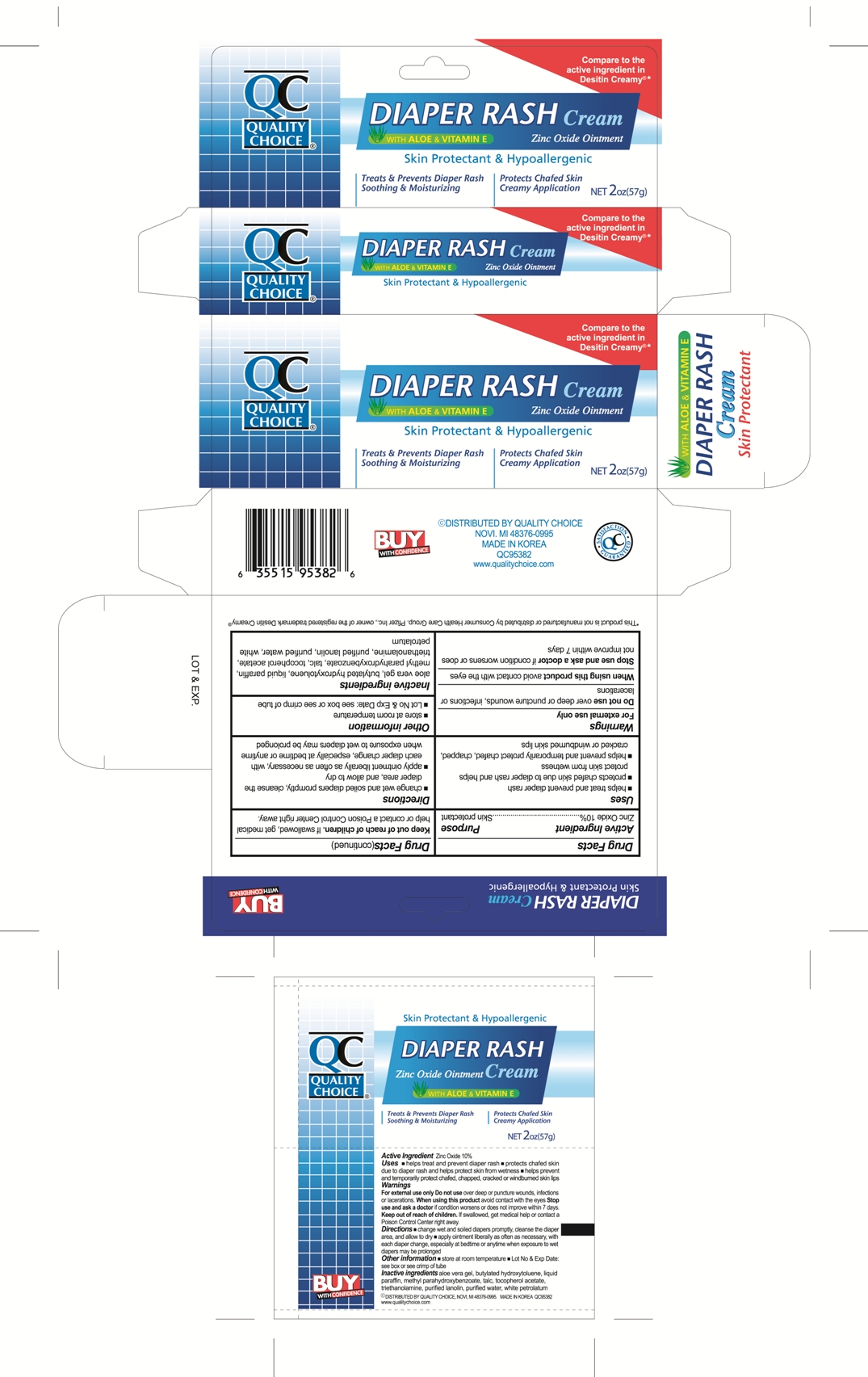 DRUG LABEL: QC Diaper Rash
NDC: 64525-5382 | Form: CREAM
Manufacturer: Quality Home Products
Category: otc | Type: HUMAN OTC DRUG LABEL
Date: 20110912

ACTIVE INGREDIENTS: ZINC OXIDE 0.10 g/1 g
INACTIVE INGREDIENTS: ALOE VERA LEAF; BUTYLATED HYDROXYTOLUENE; MINERAL OIL; METHYLPARABEN; TALC; ALPHA-TOCOPHEROL ACETATE; TROLAMINE; LANOLIN; WATER; PETROLATUM

Drug Facts

Active ingredient

Zinc Oxide 10%

Purpose

Skin Protectant

Uses

- helps treat and prevent diaper rash
- protects chafed skin due to diaper rash and helps protect skin from wetness
- helps prevent and temporarily protect chafed, chapped, cracked or windburned skin lips

Warnings

For external use only

Do not use

over deep or puncture wounds, infections or lacerations

When using this product

avoid contact with the eyes

Stop use and ask a doctor

if condition worsens or does not improve within 7 days.

Keep out of reach of children.

If swallowed, get medical help or contact a Poison Control Center right away.

Directions

- change wet and soiled diapers promptly, cleanse the diaper area, and allow to dry
- apply ointment liberally as often as necessary, with each diaper change, especially at bedtime or anytime when exposure to wet diapers may be prolonged

Other information

- store at room temperature
- Lot No and Exp Date: see box or see crimp of tube

Inactive ingredients

aloe vera gel, butylated hydroxytoluene, liquid paraffin, methyl parahydroxybenzoate, talc, tocopherol acetate, triethanolamine, purified lanolin, purified water, white petrolatum

Package label

QC Diaper Rash Cream